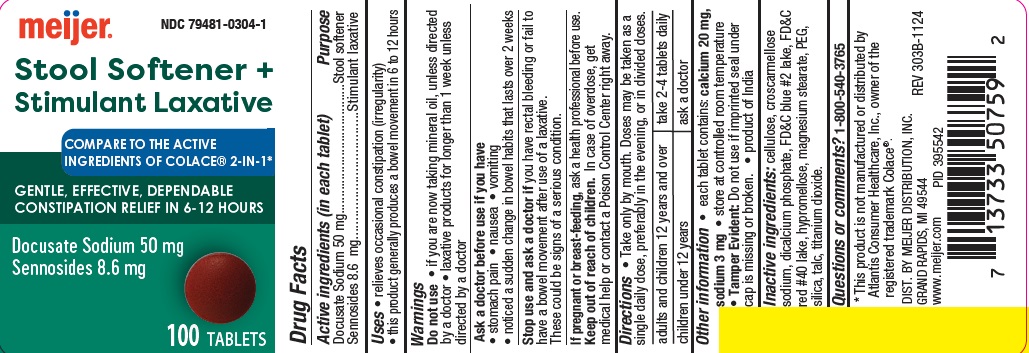 DRUG LABEL: Stool Softener plus Stimulant Laxative
NDC: 79481-0304 | Form: TABLET, FILM COATED
Manufacturer: Meijer, Inc.
Category: otc | Type: HUMAN OTC DRUG LABEL
Date: 20250324

ACTIVE INGREDIENTS: SENNOSIDES 8.6 mg/1 1; DOCUSATE SODIUM 50 mg/1 1
INACTIVE INGREDIENTS: POLYETHYLENE GLYCOL, UNSPECIFIED; HYPROMELLOSES; FD&C BLUE NO. 2; TITANIUM DIOXIDE; MAGNESIUM STEARATE; CELLULOSE, MICROCRYSTALLINE; CROSCARMELLOSE SODIUM; CALCIUM PHOSPHATE, DIBASIC, DIHYDRATE; FD&C RED NO. 40; SILICON DIOXIDE; TALC

GS 303B (304)

Active ingredient (in each tablet)

Docusate Sodium 50 mg
Sennosides 8.6 mg

Purpose

Stool softener

Stimulant laxative

Uses

- relieves occasional constipation (irregularity)

- this product generally produces bowel movement in 6 to 12 hours

Warnings

Do not use

- if you are now taking mineral oil, unless told to do so by a doctor
- laxative products for longer than 1 week unless directed by a doctor

Ask a doctor before use if you have

- stomach pain
- nausea
- vomiting
- noticed a sudden change in bowel habits that lasts over 2 weeks

Stop use and ask a doctor if you have rectal bleeding or fail to have a bowel movement after use of a laxative. These may indicate a serious condition.

If pregnant or breast-feeding, ask a health professional before use.

Keep out of reach of children. In case of overdose, get medical help or contact a Poison Control Center right away.

Directions

- Take only by mouth. Doses may be taken as a single daily dose, preferably in the evening, or in divided doses

adults and children 12 years and over | take 2-4 tablets daily
children under 12 years | ask a doctor

Other information

- each tablet contains: calcium 20 mg, sodium 3 mg
- store at controlled room temperature
- Tamper Evident: Do not use if imprinted seal under cap is missing or broken.
- product of India

Inactive ingredients

cellulose, croscarmellose sodium, dicalcium phosphate, FD&C blue #2 lake, FD&C red #40 lake, hypromellose, magnesium stearate, PEG, silica, talc, titanium dioxide.

Questions or comments?

1-800-540-3765